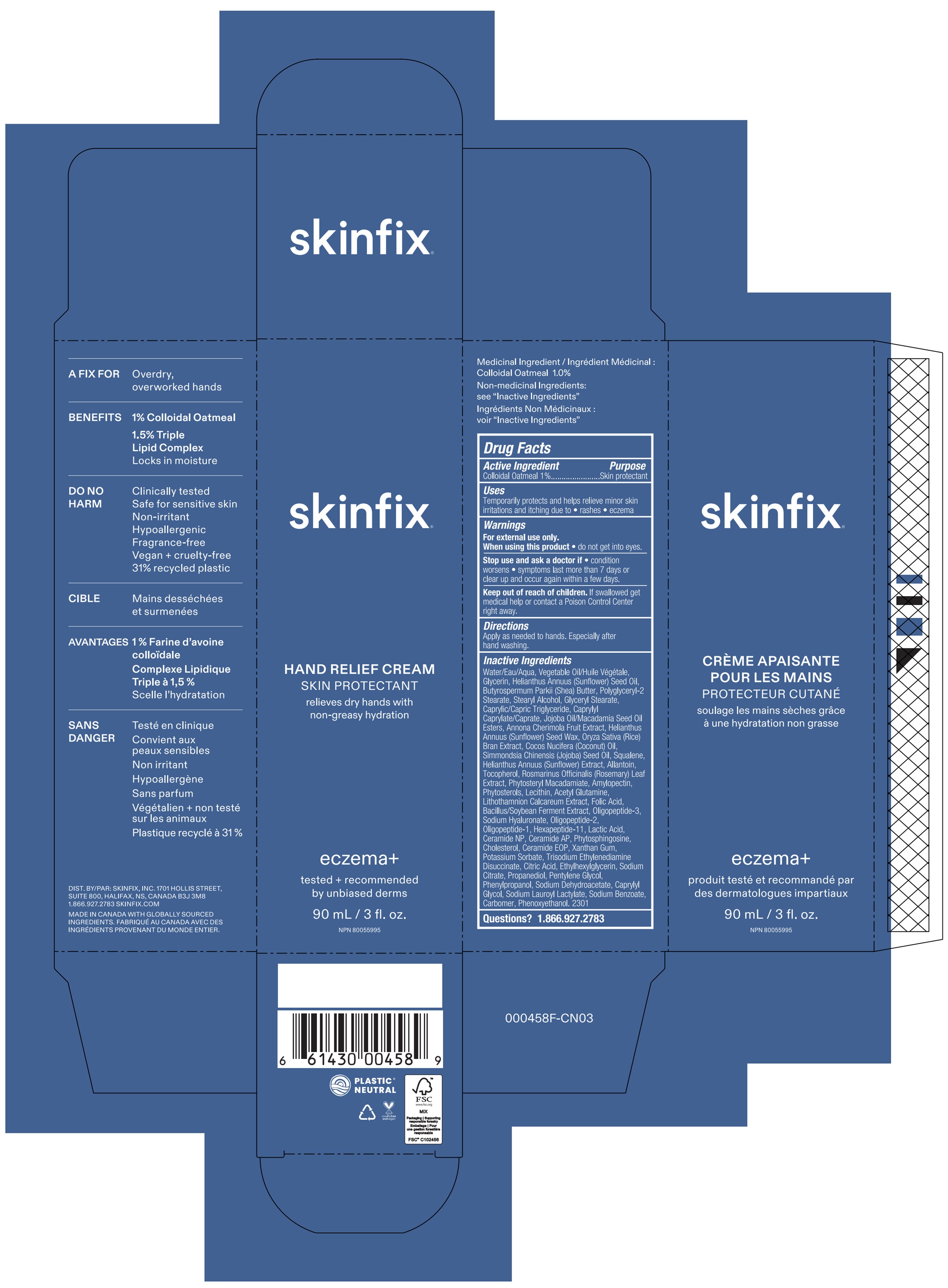 DRUG LABEL: ECZEMA HAND RELIEF
NDC: 61328-010 | Form: CREAM
Manufacturer: Skinfix, Inc.
Category: otc | Type: HUMAN OTC DRUG LABEL
Date: 20260112

ACTIVE INGREDIENTS: OATMEAL 1 g/100 g
INACTIVE INGREDIENTS: CERAMIDE 1; MACADAMIA SEED OIL GLYCERETH-8 ESTERS; PHYTOSTERYL MACADAMIATE; ACEGLUTAMIDE; PHENYLPROPANOL; LACTIC ACID; PHYMATOLITHON CALCAREUM; WATER; POLYGLYCERYL-2 STEARATE; STEARYL ALCOHOL; GLYCERYL MONOSTEARATE; PHENOXYETHANOL; POTASSIUM SORBATE; SODIUM CITRATE; LECITHIN, SOYBEAN; HEXAPEPTIDE-11; TOCOPHEROL; CAPRYLYL GLYCOL; GLYCERIN; SUNFLOWER OIL; CHERIMOYA; SUNFLOWER SEED; TRISODIUM ETHYLENEDIAMINE DISUCCINATE; ALLANTOIN; ROSEMARY; PROPANEDIOL; PENTYLENE GLYCOL; SODIUM DEHYDROACETATE; FOLIC ACID; HYALURONATE SODIUM; SODIUM LAUROYL LACTYLATE; SODIUM BENZOATE; CERAMIDE AP; PHYTOSPHINGOSINE; CHOLESTEROL; CARBOMER HOMOPOLYMER, UNSPECIFIED TYPE; SHEA BUTTER; MEDIUM-CHAIN TRIGLYCERIDES; SQUALENE; HELIANTHUS ANNUUS SEED WAX; ETHYLHEXYLGLYCERIN; CITRIC ACID MONOHYDRATE; AMYLOPECTIN, UNSPECIFIED SOURCE; CAPRYLYL CAPRYLATE/CAPRATE; RICE GERM; XANTHAN GUM; COCONUT OIL; JOJOBA OIL; CERAMIDE NP

ECZEMA HAND RELIEF

ACTIVE INGREDIENT

Colloidal Oatmeal 1%

USES

Temporarily protects and helps relieve minor skin irritations and itching due to rashes or eczema.

PURPOSE

Skin protectant

WARNINGS

For external use only.

When using this product avoid contact with eyes. if contact occurs, rinse thoroughly with water.

KEEP OUT OF REACH OF CHILDREN

If swallowed get medical help or contact a poison control center right away.

STOP USE AND ASK A DOCTOR IF

condition worsens
symptoms last more than 7 days or clear up and occur again within a few days

DIRECTIONS

Apply as needed to hands.

INACTIVE INGREDIENTS

Water/Eau/Aqua, Vegetable Oil/Huile Végétale, Glycerin, Helianthus Annuus (Sunflower) Seed Oil, Butyrospermum Parkii (Shea) Butter, Polyglyceryl-2 Stearate, Stearyl Alcohol, Glyceryl Stearate, Caprylic/Capric Triglyceride, Caprylyl Caprylate/Caprate, Jojoba Oil/Macadamia Seed Oil Esters, Annona Cherimola Fruit Extract, Helianthus Annuus (Sunflower) Seed Wax, Oryza Sativa (Rice) Bran Extract, Cocos Nucifera (Coconut) Oil, Simmondsia Chinensis (Jojoba) Seed Oil, Squalene, Helianthus Annuus (Sunflower) Extract, Allantoin, Tocopherol, Rosmarinus Officinalis (Rosemary) Leaf Extract, Phytosteryl Macadamiate, Amylopectin, Phytosterols, Lecithin, Acetyl Glutamine, Lithothamnion Calcareum Extract, Folic Acid, Bacillus/Soybean Ferment Extract, Oligopeptide-3, Sodium Hyaluronate, Oligopeptide-2, Oligopeptide-1, Hexapeptide-11, Lactic Acid, Ceramide NP, Ceramide AP, Phytosphingosine, Cholesterol, Ceramide EOP, Xanthan Gum, Potassium Sorbate, Trisodium Ethylenediamine Disuccinate, Citric Acid, Ethylhexylglycerin, Sodium Citrate, Propanediol, Pentylene Glycol, Phenylpropanol, Sodium Dehydroacetate, Caprylyl Glycol, Sodium Lauroyl Lactylate, Sodium Benzoate, Carbomer, Phenoxyethanol

QUESTIONS?

1.866.927.2783